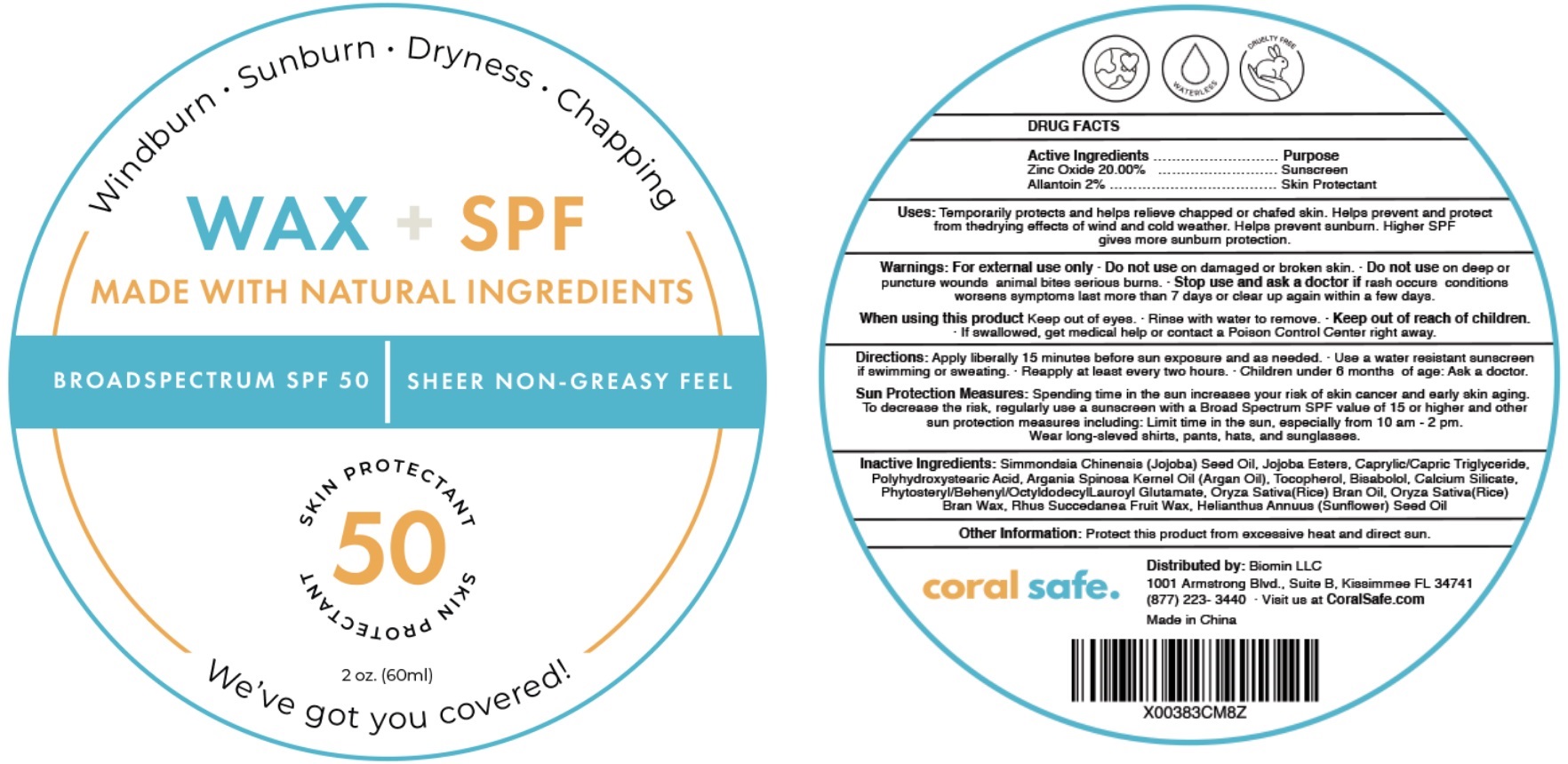 DRUG LABEL: Wax SPF 50
NDC: 82177-002 | Form: OINTMENT
Manufacturer: Biomin LLC.
Category: otc | Type: HUMAN OTC DRUG LABEL
Date: 20220602

ACTIVE INGREDIENTS: ZINC OXIDE 200 mg/1 mL; ALLANTOIN 20 mg/1 mL
INACTIVE INGREDIENTS: JOJOBA OIL; MEDIUM-CHAIN TRIGLYCERIDES; ARGAN OIL; TOCOPHEROL; LEVOMENOL; CALCIUM SILICATE; RICE BRAN OIL; RICE BRAN; SUNFLOWER OIL

Wax + SPF 50

Active Ingredients

Zinc Oxide 20.00%

Allantoin 2%

Purpose

Sunscreen

Skin Protectant

Uses:

Temporarily protects and helps relieve chapped or chafed skin. Helps prevent and protect from the drying effects of wind and cold weather. Helps prevent sunburn. Higher SPF gives more sunburn protection.

Warnings:

For external use only.

Do not use

- on damaged or broken skin.
- Do not use deep or puncture wounds animal bites serious burns.

Stop use and ask a doctor

- If rash occurs conditions worsens symptoms last more than 7 days or clear up again within a few days.

When using this product

- Keep out of eyes.
- Rinse with water to remove.

Keep out of reach of children.

- If swallowed, get medical help or contact a Poison Control Center right away.

Directions:

- Apply liberally 15 minutes before sun exposure and as needed. Use a water resistant sunscreen if swimming or sweating.
- Reapply at least every two hours.
- Children under 6 months of age: Ask a doctor.

Sun Protection Measures: Spending time in the sun increases your risk of skin cancer and early skin aging. To decrease the risk, regularly use a sunscreen with a Broad Spectrum SPF value of 15 or higher and other sun protection measures including: Limit time in the sun, especially from 10 am - 2 pm. Wear long-sleeved shirts, pants, hats, and sunglasses.

Inactive Ingredients:

Simmondsia Chinensis (Jojoba) Seed Oil, Jojoba Esters, Caprylic/Capric Triglyceride, Polyhydroxystearic Acid, Argania Spinosa Kernel Oil (Argan Oil), Tocopherol, Bisabolol, Calcium Silicate, Phytosteryl/Behenyl/Octyldodecyl Lauroyl Glutamate, Oryza Sativa (Rice) Bran Oil, Oryza Sativa (Rice) Bran Wax, Rhus Succedanea Fruit Wax, Helianthus Annuus (Sunflower) Seed Oil

Other Information:

Protect this product from excessive heat and direct sun.